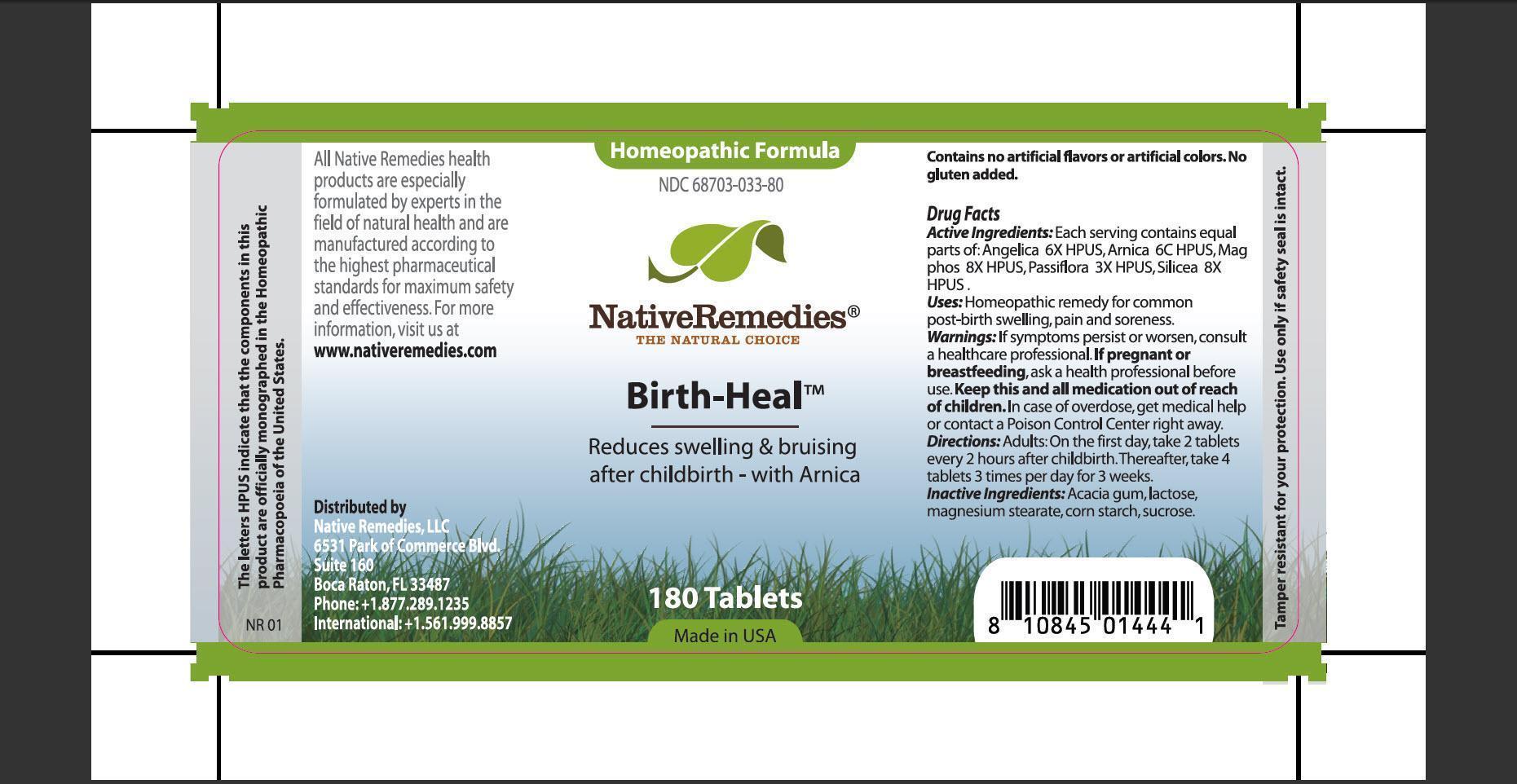 DRUG LABEL: Birth-Heal
NDC: 68703-033 | Form: TABLET
Manufacturer: Native Remedies, LLC
Category: homeopathic | Type: HUMAN OTC DRUG LABEL
Date: 20120829

ACTIVE INGREDIENTS: ANGELICA SINENSIS ROOT 6 [hp_X]/1 1; ARNICA MONTANA 6 [hp_C]/1 1; MAGNESIUM PHOSPHATE, DIBASIC TRIHYDRATE 8 [hp_X]/1 1; PASSIFLORA INCARNATA FLOWERING TOP 3 [hp_X]/1 1; SILICON DIOXIDE 8 [hp_X]/1 1
INACTIVE INGREDIENTS: ACACIA; LACTOSE; MAGNESIUM STEARATE; STARCH, CORN; SUCROSE

Birth-Heal

PURPOSE

Reduces swelling and bruising after childbirth - with Arnica

ACTIVE INGREDIENT

Active Ingredients: Each serving contains equal parts of: Angelica 6X HPUS, Arnica 6C HPUS, Mag phos 8X HPUS, Passiflora 3X HPUS, Silicea 8X HPUS.

INDICATIONS AND USAGE

Uses: Homeopathic remedy for common post-birth swelling, pain and soreness.

WARNINGS

Warnings: If symptoms persist or worsen, consult a healthcare professional.

PREGNANCY OR BREAST FEEDING

If pregnant or breastfeeding, ask a health professional before use.

KEEP OUT OF REACH OF CHILDREN

Keep this and all medication out of reach of children.

OVERDOSAGE

In case of overdose, get medical help or contact a Poison Control Center right away.

DOSAGE AND ADMINISTRATION

Directions: Adults: On first day, take 2 tablets every 2 hours after childbirth. Thereafter, take 4 tablets 3 times per day for 3 weeks.

INACTIVE INGREDIENT

Inactive Ingredients: Acacia gum, lactose, magnesium stearate, corn starch, sucrose.

PATIENT COUNSELING INFORMATION

The letters HPUS indicate that the components in this product are officially monographed in the Homeopathic Pharmacopoeia of the United States.

All Native Remedies health products are especially formulated by experts in the field of natural health and are manufactured according to the highest pharmaceutical standards for maximum safety and effectiveness. For more information, visit us at www.nativeremedies.com

Distributed by
Native Remedies, LLC
6531 Park of Commerce Blvd.
Suite 160
Boca Raton, FL 33487
Phone: +1.877.289.1235
International: +1.561.999.8857

Contains no artificial flavors or artificial colors. No gluten added.

STORAGE AND HANDLING

Tamper resistant for your protection. Use only if safety seal is intact.